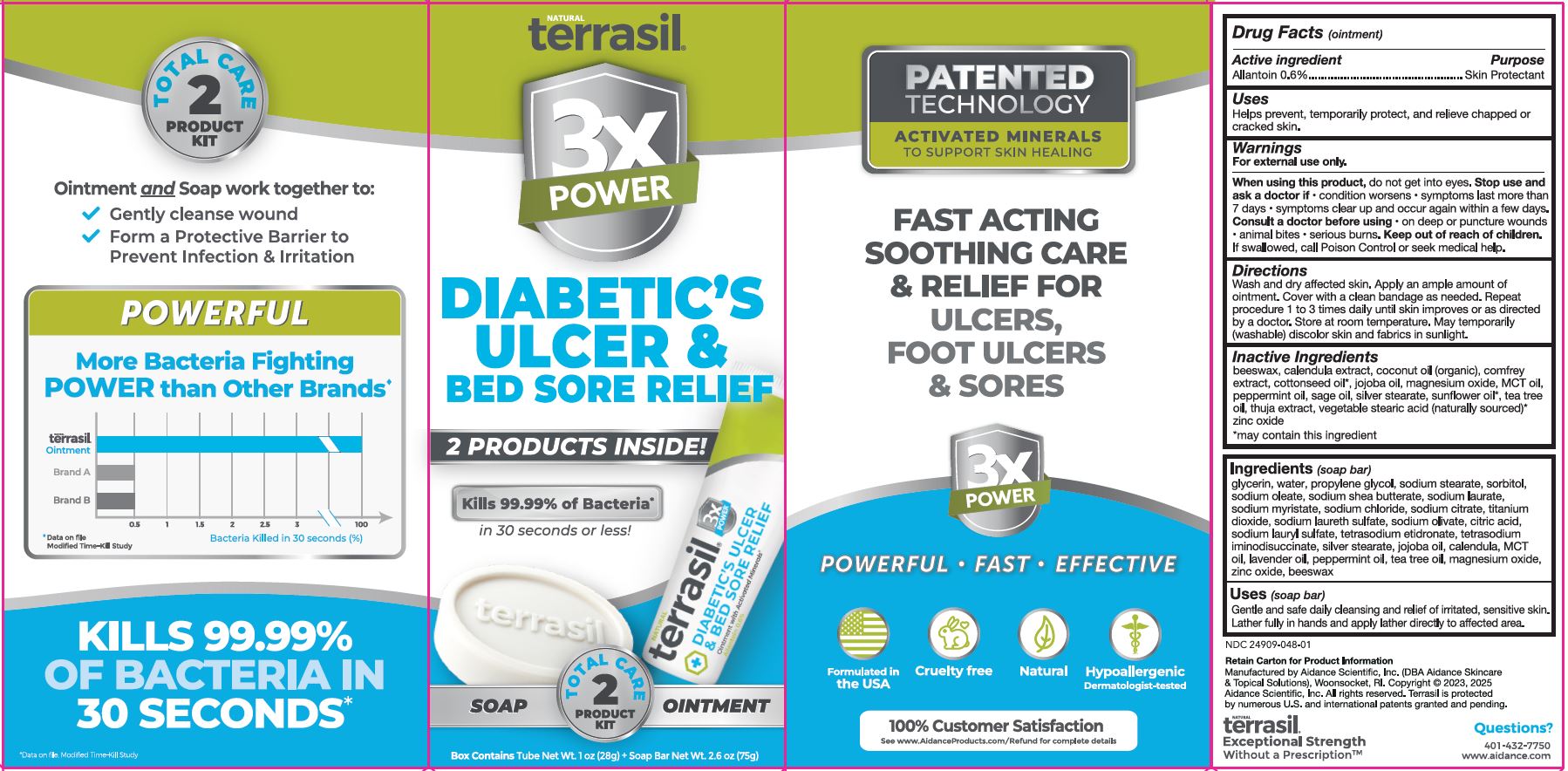 DRUG LABEL: terrasil Diabetics Ulcer and Bed Sore Relief
NDC: 24909-048 | Form: KIT | Route: TOPICAL
Manufacturer: Aidance Scientific, Inc., DBA Aidance Skincare & Topical Solutions
Category: otc | Type: HUMAN OTC DRUG LABEL
Date: 20250523

ACTIVE INGREDIENTS: ALLANTOIN 0.6 g/100 g
INACTIVE INGREDIENTS: MAGNESIUM OXIDE; PEPPERMINT OIL; SUNFLOWER OIL; ZINC OXIDE; YELLOW WAX; COMFREY ROOT; JOJOBA OIL; PALM OIL; COCONUT OIL; COTTONSEED OIL; SAGE OIL; THUJA OCCIDENTALIS LEAF; CALENDULA OFFICINALIS FLOWER; STEARIC ACID; TEA TREE OIL; SILVER STEARATE

24909-048 terrasil Diabetic's Ulcer & Bed Sore Relief Kit

Active Ingredient

Allantoin 0.6%

Purpose

Skin Protectant

Uses

Helps prevent, temporarily protect, and relieve chapped or cracked skin.

Warnings

For external use only.
When using this product, do not get into eyes.

Stop use and ask a doctor if

- condition worsens
- symptoms last more than 7 days
- symptoms clear up and occur again within a few days.

Consult a doctor before using

- on deep or puncture wounds
- animal bites
- serious burns

Keep out of reach of children.

OTHER SAFETY INFORMATION

If swallowed, call Poison Control or seek medical help.

Directions

Wash and dry affected skin. Apply an ample amount of ointment. Cover with a clean bandage. Repeat procedure 1 to 3 times daily until skin improves or as directed by a doctor.

STORAGE AND HANDLING

Store at room temperature.

May temporarily (washable) discolor skin and fabrics in sunlight.

Inactive Ingredients

beeswax, calendula extract, coconut oil (organic), comfrey extract, cottonseed oil*, jojoba oil, magnesium oxide, MCT oil, peppermint oil, sage oil, silver stearate, sunflower oil*, tea tree oil, thuja extract, vegetable stearic acid (naturally sourced)*, zinc oxide

Soap Bar (non-medicated)

Uses
Gentle and safe daily cleansing and relief of irritated, sensitive skin. Lather fully in hands and apply lather directly to affected area.

Ingredients
glycerin, water, propylene glycol, sodium stearate, sorbitol, sodium oleate, sodium shea butterate, sodium laurate, sodium myristate, sodium chloride, sodium citrate, titanium dioxide, sodium laureth sulfate, sodium olivate, citric acid, sodium lauryl sulfate, tetrasodium etidronate, tetrasodium iminodisuccinate, silver stearate, jojoba oil, calendula, MCT oil, lavender oil, peppermint oil, tea tree oil, magnesium oxide, zinc oxide, beeswax

Questions?

401-432-7750

www.aidance.com